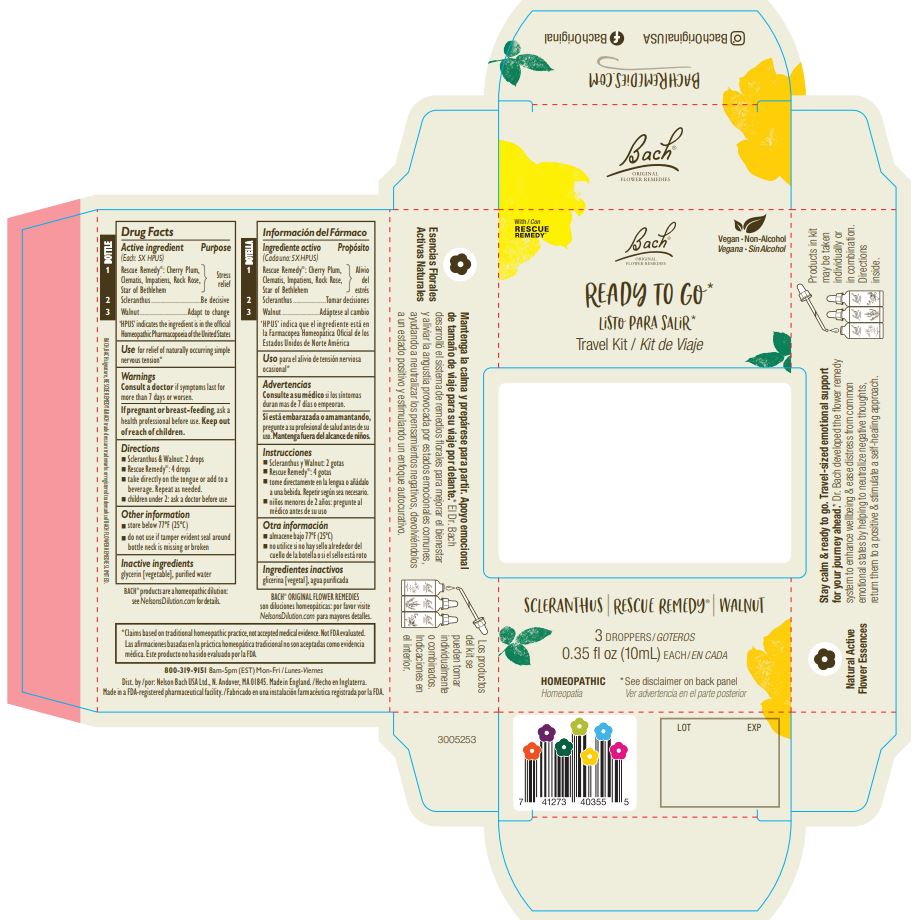 DRUG LABEL: Bach Ready to Go Travel Kit
NDC: 57687-316 | Form: KIT | Route: ORAL
Manufacturer: Nelson Bach USA Limited
Category: homeopathic | Type: HUMAN OTC DRUG LABEL
Date: 20231016

ACTIVE INGREDIENTS: SCLERANTHUS ANNUUS FLOWERING TOP 5 [hp_X]/0.095 mL; CLEMATIS VITALBA FLOWER 5 [hp_X]/0.095 mL; HELIANTHEMUM NUMMULARIUM FLOWER 5 [hp_X]/0.095 mL; PRUNUS CERASIFERA FLOWER 5 [hp_X]/0.095 mL; IMPATIENS GLANDULIFERA FLOWER 5 [hp_X]/0.095 mL; ORNITHOGALUM UMBELLATUM WHOLE 5 [hp_X]/0.095 mL; JUGLANS REGIA FLOWERING TOP 5 [hp_X]/0.095 mL
INACTIVE INGREDIENTS: WATER; GLYCERIN; WATER; GLYCERIN; WATER; GLYCERIN

Bach Ready to Go Travel Kit

ACTIVE INGREDIENT

Active ingredient (Each 5X HPUS)...................................................................................................... Purpose

Bottle 1: Rescue Remedy®: Cherry Plum, Clematis, Impatiens, Rock Rose, Star of Bethlehem.........Stress relief

Bottle 2: Scleranthus.............................................................................................................................Be decisive

Bottle 3: Walnut........................................................... .........................................................................Adapt to change

'HPUS’ indicates the ingredient is in the official Homeopathic Pharmacopoeia of the United States

Use

For relief of naturally occuring simple nervous tension

Warnings

Consult a doctor if symptoms last for more than 7 days or worsen.

PREGNANCY OR BREAST FEEDING

If pregnant or breast-feeding, ask a health professional before use.

Keep out of reach of children.

Directions

■ Scleranthus & Walnut: 2 drops
■ Rescue Remedy®: 4 drops
■ take directly on the tongue or add to a beverage. Repeat as needed.
■ children under 2: ask a doctor before use

Other information

■ store below 77ºF (25ºC)
■ do not use if tamper evident seal around bottle neck is missing or broken

Inactive ingredients

glycerin [vegetable], purified water